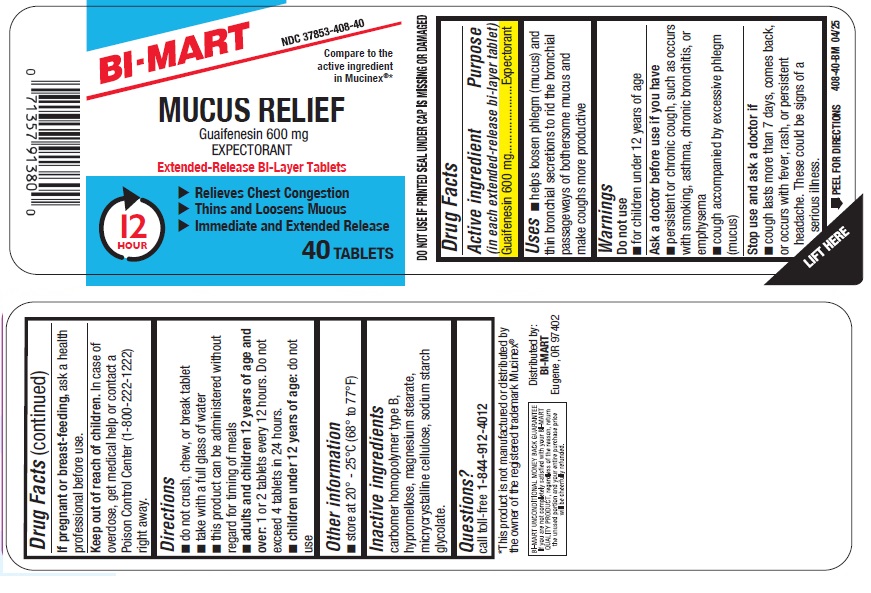 DRUG LABEL: Mucus Relief
NDC: 37835-408 | Form: TABLET
Manufacturer: Bi-Mart
Category: otc | Type: HUMAN OTC DRUG LABEL
Date: 20250501

ACTIVE INGREDIENTS: GUAIFENESIN 600 mg/1 1
INACTIVE INGREDIENTS: CARBOMER HOMOPOLYMER TYPE B (ALLYL SUCROSE CROSSLINKED); HYPROMELLOSE 2910 (5 MPA.S); SODIUM STARCH GLYCOLATE TYPE A; MAGNESIUM STEARATE; MICROCRYSTALLINE CELLULOSE

Active ingredient (in each extended-release bi-layer tablet)

Guaifenesin 600 mg

Purpose

Expectorant

Uses

- helps loosen phlegm (mucus) and thin bronchial secretions to rid the bronchial passageway of bothersome mucus and make coughs more productive

Warnings

Do not use

- for children under 12 years of age

Ask a doctor before use if you have

- persistent or chronic cough such as occurs with smoking, asthma, chronic bronchitis or emphysema
- cough accompanied by excessive phlegm (mucus)

Stop use and ask a doctor if

- cough lasts more than 7 days, comes back, or occurs with fever, rash, or persistent headache. These could be signs of a serious illness.

PREGNANCY OR BREAST FEEDING

If pregnant or breast-feeding, ask a health professional before use.

Keep out of reach of children.

In case of overdose, get medical help or contact a Poison Control Center (1-800-222-1222) right away.

Directions

- do not crush, chew, or break tablet
- take with a full glass of water
- this product can be administered without regard for timing of meals
- adults and children 12 years of age and over: 1 or 2 tablet every 12 hours. Do not exceed 4 tablets in 24 hours.
- children under 12 years of age: do not use

Other information

- store at 20-25°C (68-77°F)
- DO NOT USE IF PRINTED SEAL UNDER CAP IS MISSING OR DAMAGED

Inactive ingredients

carbomer homopolymer type B, hypromellos, magnesium stearate, microcrystalline cellulose, sodium starch glycolate.

Questions?

call toll-free 1-844-912-4012

Distributed by:

BI-MART

Eugene, OR 97402